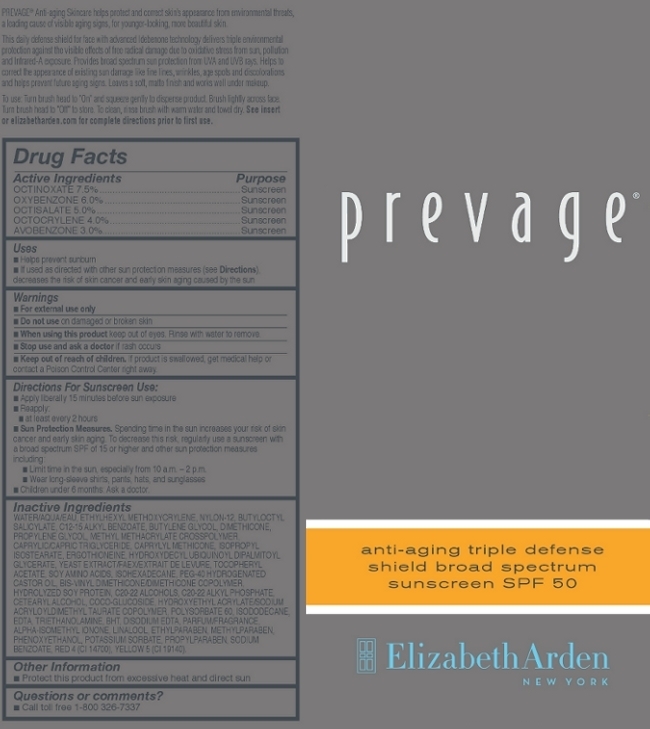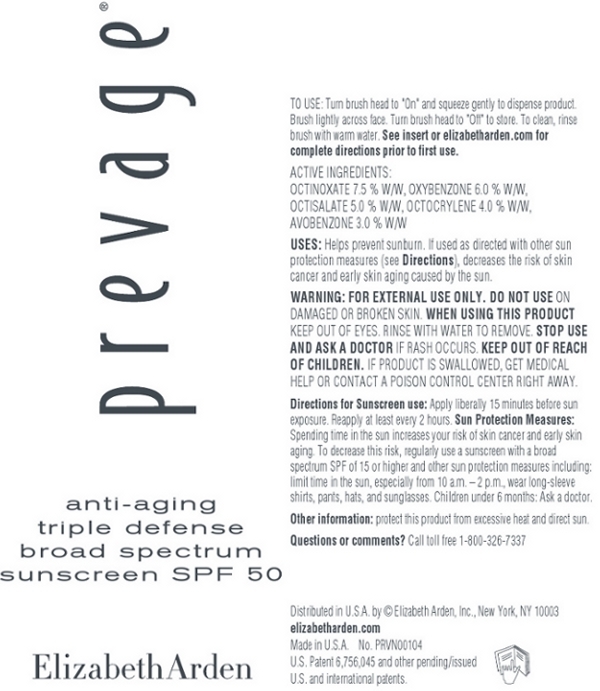 DRUG LABEL: Prevage Anti Agining Triple Defense Shield Broad Spectrum Sunscreen SPF 50
NDC: 67938-0990 | Form: LOTION
Manufacturer: Elizabeth Arden, Inc
Category: otc | Type: HUMAN OTC DRUG LABEL
Date: 20130501

ACTIVE INGREDIENTS: OCTINOXATE 75 mg/50 mL; OXYBENZONE 60 mg/50 mL; OCTISALATE 50 mg/50 mL; OCTOCRYLENE 40 mg/50 mL; AVOBENZONE 30 mg/50 mL
INACTIVE INGREDIENTS: WATER; NYLON-12; BUTYLOCTYL SALICYLATE; ALKYL (C12-15) BENZOATE; BUTYLENE GLYCOL; DIMETHICONE; PROPYLENE GLYCOL; MEDIUM-CHAIN TRIGLYCERIDES; CAPRYLYL TRISILOXANE; ISOPROPYL ISOSTEARATE; ERGOTHIONEINE; YEAST; .ALPHA.-TOCOPHEROL ACETATE; ISOHEXADECANE; POLYOXYL 40 HYDROGENATED CASTOR OIL; C20-22 ALCOHOLS; C20-22 ALKYL PHOSPHATE; CETOSTEARYL ALCOHOL; COCO GLUCOSIDE; POLYSORBATE 60; ISODODECANE; EDETIC ACID; BUTYLATED HYDROXYTOLUENE; EDETATE DISODIUM; ISOMETHYL-.ALPHA.-IONONE; ETHYLPARABEN; METHYLPARABEN; PHENOXYETHANOL; POTASSIUM SORBATE; PROPYLPARABEN; SODIUM BENZOATE

BB0990

DESCRIPTION

PREVAGE Anti-aging Skincare helps protect and correct skin’s appearance from environmental threats, a leading cause of visible aging signs, for younger-looking, more beautiful skin. This daily defense shield for face with advanced Idebenone technology delivers triple environmental protection against the visible effects of free radical damage due to oxidative stress from sun, pollution and Infrared-A exposure. Provides broad spectrum sun protection from UVA and UVB rays. Helps to correct the appearance of existing sun damage like fine lines, wrinkles, age spots and discolorations and helps prevent future aging signs. Leaves a soft, matte finish and works well under makeup.

INDICATIONS AND USAGE

To Use: Turn brush head to "On" and squeeze gently to dispense product. Brush lightly across face. Turn brush head to "Off" to store. To clean, rinse brush with warm water and towel dry.

Directions For Sunscreen Use:Apply liberally 15 minutes before sun exposure. Reapply at least every 2 hours

Sun Protection Measures. Spending time in the sun increases your risk of skin cancer and early skin aging. To decrease this risk, regularly use a sunscreen with a broad spectrum SPF of 15 or higher and other sun protection measures including: Limit time in the sun, especially from 10 a.m. – 2 p.m.. Wear long-sleeve shirts, pants, hats, and sunglasses

WARNINGS

For external use only

Do not use on damaged or broken skin

When using this product keep out of eyes. Rinse with water to remove.

Stop use and ask a doctor if rash occurs

OTC - ACTIVE INGREDIENT

Active Ingredients: Oxtinoxate 7.5%, Oxybenzone 6.0%, Octisalate 5.0%, Oxtocrylene 4.0%, Avobenzone 3.0%

INACTIVE INGREDIENT

Inactive Ingredients: Water/Aqua/Eau, Ethylhexyl Methoxycrylene, Nylon-12, Butyloctyl Salicylate, C12-15 Alkyl Benzoate, Butylene Glycol, Dimethicone, Propylene Glycol, Methyl Methacrylate Crosspolymer, Caprylic/Capric Triglyceride, Caprylyl Methicone, Isopropyl Isostearate, Ergothioneine, Hydroxydecyl Ubiquinoyl Dipalmitoyl Glycerate, Yeast Extract/Faex/Extrait de Levure, Tocopheryl Acetate, Soy Amino Acids, Isohexadecane, PEG-40 Hydrogenated Castor Oil, BIS-Vinyl Dimethicone/Dimethicone Copolymer, Hydrolyzed Soy Protein, C20-22 Alocohols, C20-22 Alkyl Phosphate, Cetearyl Alcohol, Coco-Glucoside, Hydroxyethyl Acrylate/Sodium Acryloyldimethyl Taurate Copolymer, Polysorbate 60, Isododecane EDTA, Triethanolamine, BHT, Disodium EDTA, Parfum/Fragrance, Alpha-Isomethyl Ionone, Linalool, Ethylparaben, Methylparaben, Phenoxyethanol, Potassium Sorbate, Propylparaben, Sodium Benzoate, Red 4 (CI 14700), Yellow 5 (CI 19140).

DOSAGE AND ADMINISTRATION

Apply to skin.

OTC - KEEP OUT OF REACH OF CHILDREN

Keep out of reach of children. If product is swallowed, get medical help or contact a Poison Control Center right away.

OTC - PURPOSE

Provides SPF 50 Sun Protection.

OTC - WHEN USING

Keep out of eyes.